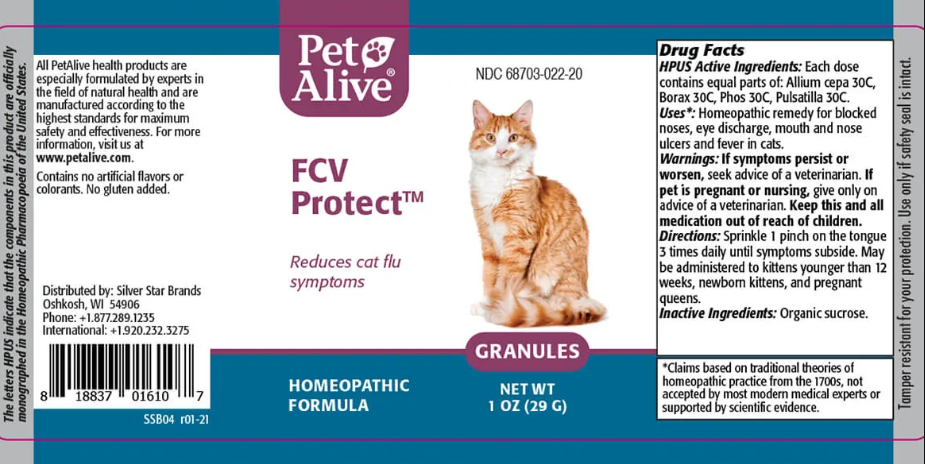 DRUG LABEL: FCV Protect
NDC: 68703-022 | Form: GRANULE
Manufacturer: SILVER STAR BRANDS
Category: homeopathic | Type: OTC ANIMAL DRUG LABEL
Date: 20251212

ACTIVE INGREDIENTS: ONION 30 [hp_C]/20 mg; SODIUM BORATE 30 [hp_C]/20 mg; PHOSPHORUS 30 [hp_C]/20 mg; PULSATILLA VULGARIS 30 [hp_C]/20 mg
INACTIVE INGREDIENTS: SUCROSE

FCV Protect

PURPOSE

Reduces cat flu symptoms

ACTIVE INGREDIENT

HPUS Active Ingredients: Each dose contains equal parts of:

Allium cepa 30C

Borax 30C

Phos 30C

Pulsatilla 30С

INDICATIONS AND USAGE

Uses: Homeopathic remedy for blocked noses, eye discharge, mouth and nose ulcers and fever in cats.

WARNINGS

Warnings: If symptoms persist or worsen, seek advice of a veterinarian.

PREGNANCY OR BREAST FEEDING

If pet is pregnant or nursing, give only on advice of a veterinarian.

KEEP OUT OF REACH OF CHILDREN

Keep this and all medication out of reach of children.

DOSAGE AND ADMINISTRATION

Directions: Sprinkle 1 pinch on the tongue 3 times daily until symptoms subside. May be administered to kittens younger than 12 weeks, newborn kittens, and pregnant queens.

Inactive Ingredients: Organic sucrose.

INFORMATION FOR OWNERS/CAREGIVERS

The letters HPUS indicate that the components in this products are officially monographed in the Homeopathic Pharmacopoeia of the United States.

All PetAlive health products are especially formulated by experts in the field of natural health and are manufactured according to the highest standards for maximum safety and effectiveness. For more information, visit us at www.petalive.com.

Contains no artificial flavors or colorants. No gluten added.

Distributed by: Silver Star Brands
Oshkosh, WI 54906
Phone: +1.877.289.1235
International: +1.920.232.3275

STORAGE AND HANDLING

Tamper resistant for your protection. Use only if safety seal is intact.